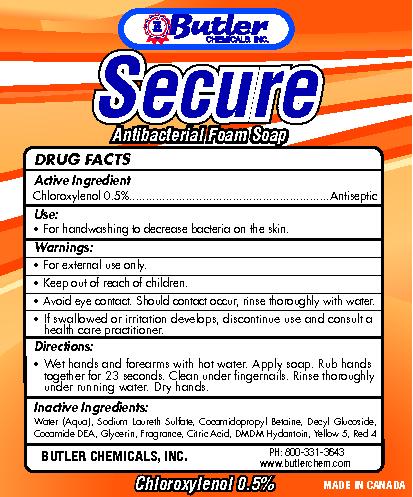 DRUG LABEL: secure
NDC: 50157-200 | Form: AEROSOL, FOAM
Manufacturer: Brands International
Category: otc | Type: HUMAN OTC DRUG LABEL
Date: 20120424

ACTIVE INGREDIENTS: CHLOROXYLENOL .5 mL/100 mL
INACTIVE INGREDIENTS: WATER; SODIUM LAURETH SULFATE; COCAMIDOPROPYL BETAINE; DECYL GLUCOSIDE; COCO DIETHANOLAMIDE; GLYCERIN; CITRIC ACID MONOHYDRATE; DMDM HYDANTOIN; FD&C  YELLOW NO. 5; FD&C RED NO. 4

Secure Antibacterial Foam

Active Ingredient chloroxylenol 0.5% antiseptic

PURPOSE

Antiseptic

Keep out of reach of children.

INDICATIONS AND USAGE

Use: For handwashing to decrease bacteria on the skin.

Warnings:
For external use only

Keep out of reach of children

Avoid eye contact. Should contact occur, rinse thoroughly with water.

If swallowed or irritation develops, discontinue use and consult a health care practitioner.

Directions:

Wet hands and forearms with hot water. Apply soap. Rub hands together for 23 seconds. Clean under fingernails. Rinse thoroughly under running water. Dry hands.

Inactive Ingredients:
water (Aqua), Sodium Laureth Sulfate, Cocamidopropyl Betaine, Decyl Glucoside, Cocamide DEA, Glycerin, Fragrance, Citric Acid, DMDM Hydantoin, Yellow 5, Red 4

PACKAGE LABEL

Butler Chemicals Inc

Secure Antibacterial Foam Soap

Butler Chemicals, Inc

PH: 800-331-3643www.butlerchem.com

Chloroxylenol 0.5% Made in Canada